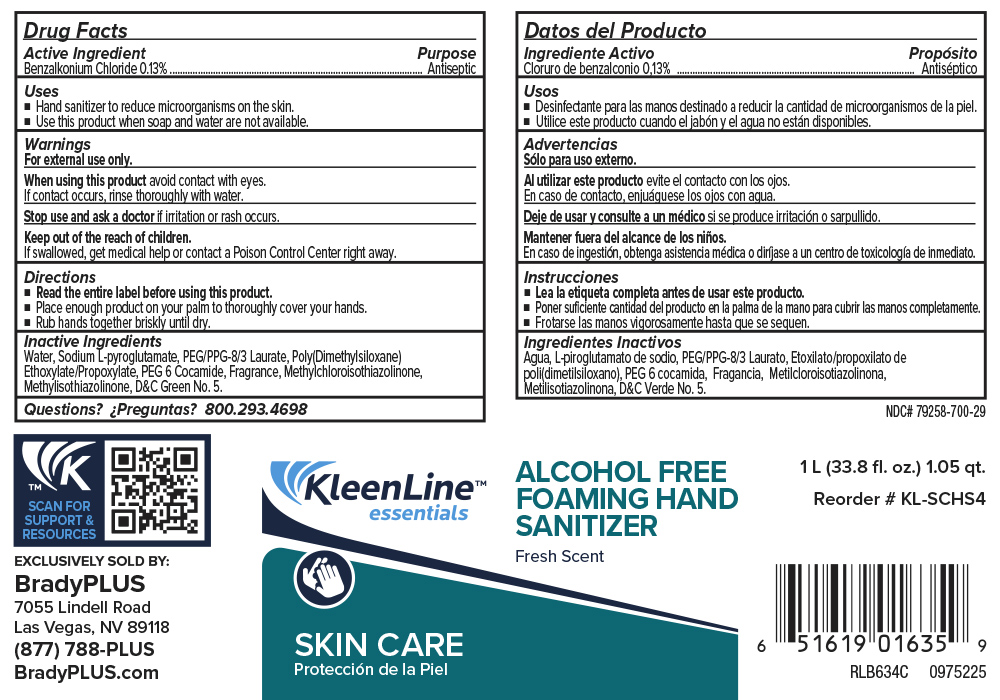 DRUG LABEL: KleenLine Essentials Alcohol Free Foaming Hand Sanitizer
NDC: 79258-700 | Form: SOAP
Manufacturer: Brady Industries
Category: otc | Type: HUMAN OTC DRUG LABEL
Date: 20251008

ACTIVE INGREDIENTS: BENZALKONIUM CHLORIDE 1.3 mg/1 mL
INACTIVE INGREDIENTS: METHYLISOTHIAZOLINONE; PEG/PPG-15/15 ALLYL ETHER ACETATE; .ALPHA.-PINENE; D&C GREEN NO. 5; .BETA.-CITRONELLOL, (+/-)-; BUTYLPHENYL METHYLPROPIONAL; METHYL DIHYDROJASMONATE (SYNTHETIC); .ALPHA.-HEXYLCINNAMALDEHYDE; ALLYL CYCLOHEXANEPROPIONATE; 2,4-DIMETHYL-3-CYCLOHEXENE CARBOXALDEHYDE; .GAMMA.-TERPINENE; SODIUM PIDOLATE; WATER; HEXYL SALICYLATE; 2-METHYL-3-(P-METHOXYPHENYL)PROPANAL; LINALOOL; OCTOXYNOL-13; PEG-8 LAURATE; METHYLCHLOROISOTHIAZOLINONE; HEXAMETHYLINDANOPYRAN; PEG-6 COCAMIDE; LIMONENE, (+)-; NEROL; GERANIOL

KleenLine Essentials Alcohol Free Foaming Hand Sanitizer

Active Ingredient

Benzalkonium Chloride .13%

Purpose

Antibacterial

Warnings

For external use only.

When using this product avoid contact with eyes.

If contact occurs, rinse thoroughly with water.

Stop use and ask a doctor if irritation or rash occurs.

Keep out of reach of children.

If swallowed get mediccal help or contact a Poison Control Center right away.

Directions

Read the entire label before using this product.

Place enough product on your palm to thoroughly cover your hands.

Rub hand together briskly until dry.

Inactive Ingredients

Water, Sodium L-pyroglutamate, PEG/PPG-8/3 Laurate, Polu(Dimethylsiloxane) Ethoxylate/Propoxylate, PEG 6 Cocamide, Fragrance, Methylchloroisothiazolinone, Methylisothiazolinone, D&C Green No. 5

Questions

Questions? 888-GO-BETCO (888-462-3826)

Purpose

Antibacterial

Keep out of Reach of Children

Warnings

For external use only.

When using this product avoid contact with eyes.

If contact occurs, rinse thoroughly with water.

Stop use and ask a doctor if irritation or rash occurs.

Keep out of reach of children.

If swallowed get mediccal help or contact a Poison Control Center right away.